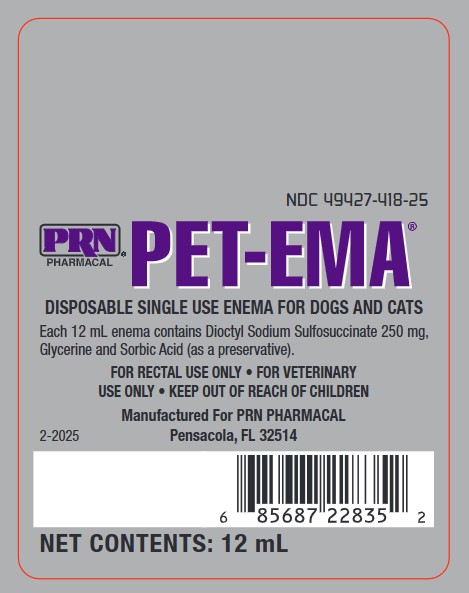 DRUG LABEL: PET-EMA
NDC: 49427-418 | Form: ENEMA
Manufacturer: Pegasus Laboratories, Inc
Category: animal | Type: OTC ANIMAL DRUG LABEL
Date: 20251229

ACTIVE INGREDIENTS: DOCUSATE SODIUM 250 mg/12 mL

DESCRIPTION

12 mL Syringe Enema for Dogs and Cats

Each syringe contains 12 mL of a solution of Dioctyl Sodium Sulfosuccinate 250 mg in Glycerin, with Sorbic Acid (as a preservative).

Stimulates the mucosa of the lower bowel and rectum; softens hardened fecal matter; lubricates the rectal wall.

USES:

As an aid in maintaining healthy lower bowel function.

DIRECTIONS FOR USE:

Remove tip cap and gently insert nozzle into rectum. If desired, nozzle can be lubricated prior to insertion. Slowly depress syringe plunger to express contents. Treatment may be repeated in one hour if necessary.

PRECAUTIONS

Not for human use

For rectal use only

For veterinary use only

Keep out of reach of children

Store in a cool dry place